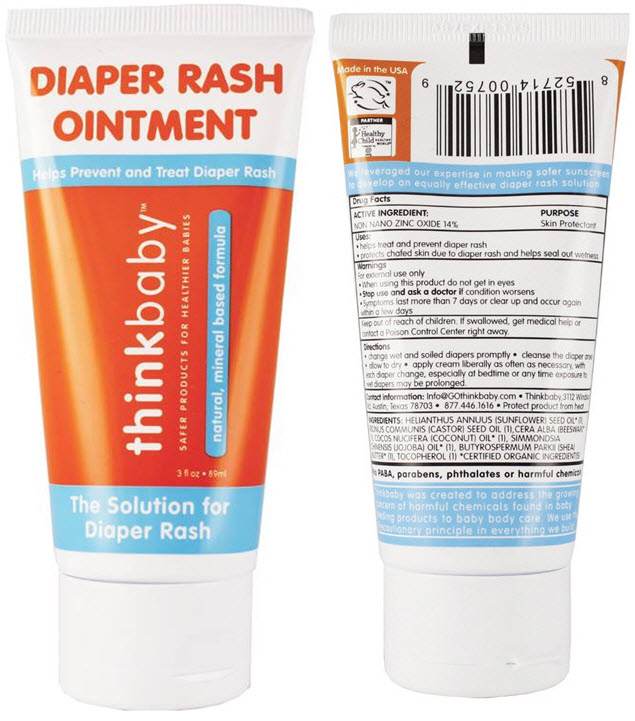 DRUG LABEL: Thinkbaby 
NDC: 60781-2018 | Form: CREAM
Manufacturer: thinkOperations,LLC
Category: otc | Type: HUMAN OTC DRUG LABEL
Date: 20200123

ACTIVE INGREDIENTS: ZINC OXIDE 140 mg/1 mL
INACTIVE INGREDIENTS: SUNFLOWER OIL; CASTOR OIL; WHITE WAX; COCONUT OIL; JOJOBA OIL; SHEA BUTTER; TOCOPHEROL

Thinkbaby™
Diaper Rash Ointment

Drug Facts

ACTIVE INGREDIENT

NON NANO ZINC OXIDE 14%

PURPOSE

Skin Protectant

Uses

- helps treat and prevent diaper rash
- protects chafed skin due to diaper rash and helps seal out wetness

Warnings

For external use only

- When using this product do not get in eyes

- Stop use and ask a doctor if condition worsens
- Symptoms last more than 7 days or clear up and occur again within a few days

Keep out of reach of children. If swallowed, get medical help or contact a Poison Control Center right away.

Directions

- change wet and soiled diapers promptly
- cleanse the diaper area
- allow to dry
- apply cream liberally as often as necessary, with each diaper change, especially at bedtime or any time exposure to wet diapers may be prolonged.

Contact information

Info@GOthinkbaby.com • Thinkbaby,3112 Windsor Rd, Austin, Texas 78703 • 877.446.1616 • Protect product from heat

INGREDIENTS

HELIANTHUS ANNUUS (SUNFLOWER) SEED OIL [CERTIFIED ORGANIC INGREDIENT(S)natural, mineral based formula] (1), RICINUS COMMUNIS (CASTOR) SEED OIL (1),CERA ALBA (BEESWAX) (1), COCOS NUCIFERA (COCONUT) OIL (1), SIMMONDSIA CHINENSIS (JOJOBA) OIL (1), BUTYROSPERMUM PARKII (SHEA) BUTTER (1), TOCOPHEROL (1)

PRINCIPAL DISPLAY PANEL - 89 ml Tube Label

DIAPER RASH
OINTMENT

Helps Prevent and Treat Diaper Rash

thinkbaby™

SAFER PRODUCTS FOR HEALTHIER BABIES

natural, mineral based formula

3 fl oz • 89ml

The Solution for
Diaper Rash